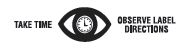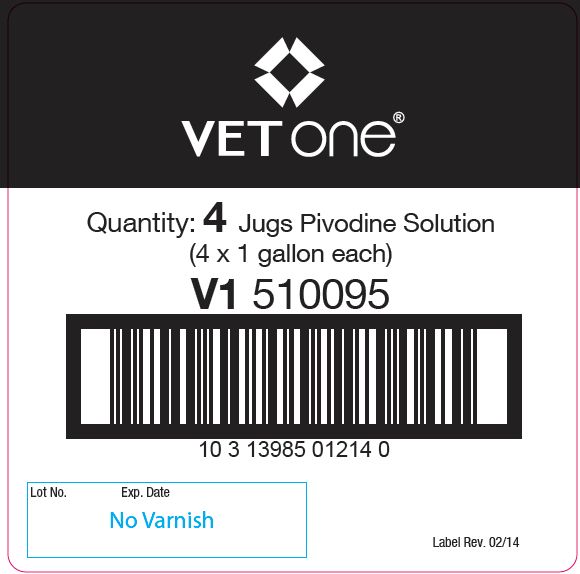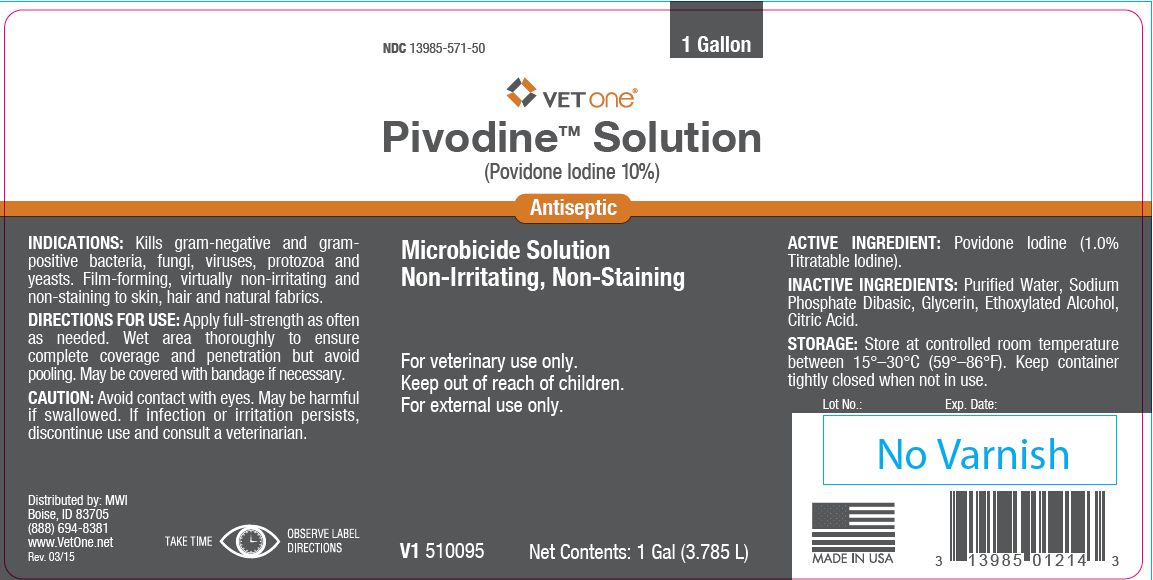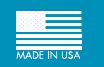 DRUG LABEL: Pivodine
NDC: 13985-571 | Form: SOLUTION
Manufacturer: MWI/Vet One
Category: animal | Type: OTC ANIMAL DRUG LABEL
Date: 20241115

ACTIVE INGREDIENTS: POVIDONE-IODINE 65.9 g/1 L

PivodineTM Solution
(Povidone Iodine 10%)
Antiseptic

PURPOSE

Microbicide Solution Non-Irritating, Non-Staining

KEEP OUT OF REACH OF CHILDREN

For veterinary use only.
Keep out of reach of children.
For external use only.

INDICATIONS:

Kills gram-negative and grampositive bacteria, fungi, viruses, protozoa and yeasts. Film-forming, virtually non-irritating and non-staining to skin, hair and natural fabrics.

DIRECTIONS FOR USE:

Apply full-strength as often as needed. Wet area thoroughly to ensure complete coverage and penetration but avoid pooling. May be covered with bandage if necessary.

CAUTION:

Avoid contact with eyes. May be harmful if swallowed. If infection or irritation persists, discontinue use and consult a veterinarian.

ACTIVE INGREDIENT:

Povidone Iodine (1.0% Titratable Iodine).

INACTIVE INGREDIENTS:

Purified Water, Sodium Phosphate Dibasic, Glycerin, Ethoxylated Alcohol, Citric Acid.

STORAGE:

Store at controlled room temperature between 15°–30°C (59°–86°F). Keep container tightly closed when not in use.

Net Contents:

1 Gal (3.785 L) V1 510095

INFORMATION FOR OWNERS/CAREGIVERS

Distributed by: MWI
Boise, ID 83705
(888) 694-8381
www.VetOne.net
Rev. 03/15